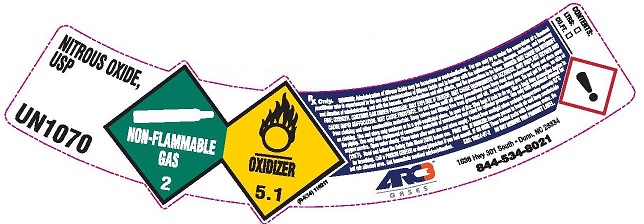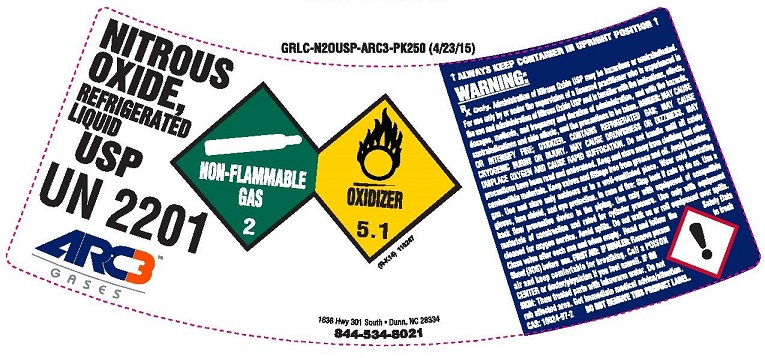 DRUG LABEL: Nitrous Oxide
NDC: 49575-003 | Form: GAS
Manufacturer: Machine & Welding Supply Company dba Arc3 Gases South
Category: prescription | Type: HUMAN PRESCRIPTION DRUG LABEL
Date: 20251202

ACTIVE INGREDIENTS: NITROUS OXIDE 990 mL/1 L

nitrous oxide

PACKAGE LABEL

NITROUS OXIDE USP UN1070 NON-FLAMMABLE GAS 2 OXIDIZER 5.1
Rx only. WARNING: Administration of Nitrous Oxide may be hazardous or contraindicated. For use only by or under the supervision of a licensed practitioner who is experienced in the use and administration of Nitrous Oxide and is familiar with the indications, effects, dosages, methods, and frequency and duration of administration, and with the hazards, contraindications and side effects, and the precautions to be taken. DANGER: MAY CAUSE OR INTENSIFY FIRE; OXIDIZER CONTAINS GAS UNDER PESSURE; MAY EXPLODE IF HEATED. MAY CUASE DROWSINESS OR DIZZINESS. MAY DISPLACE OXYGEN AND CAUSE RAPID SUFFOCATION. MAY CAUSE FROSTBITE. Do not handle until all safety precautions have been read and understood. Keep and store away from clothing and other combustible materials. Keep valves and fittings free from grease and oil. Avoid breathing gas. Do not put in eyes on skin or on clothing. Use and store only outdoors or in a well-ventilated place. In case of fire: stop leak if safe to do so. Use a back flow preventive device in the piping. Use only with equipment of compatible materials of construction and rated for cylinder pressure. Use only with equipment cleaned for oxygen service. Open valve slowly. Close valve after each use and when empty. Protect from sunlight when ambient temperature exceeds 52 degrees C (125 degrees F). Read and follow the Safety Data Sheet (SDS) before use. FIRST AID: IF INHALED: Remove person to fresh air and keep comfortable for breathing. Call a POISON CENTER or doctor/physician if you feel unwell. IF ON SKIN: Thaw frosted parts with lukewarm water. Do not rub affected area. Get immediate medical advice/attention. CAS: 10024-97-2 DO NOT REMOVE THIS LABEL.
ARC3 GASES 1636 Hwy 301 South Dunn, NC 28334 844-534-8021

PACKAGE LABEL

NITROUS OXIDE, REFRIGERATED LIQUID USP UN2201 ARC3 GASES NON-FLAMMABLE GAS 2 OXIDIZER 5.1 1636 Hwy 301 South . Dunn, NC 28334 844-534-8021
ALWAYS KEEP CONTAINER IN UPRIGHT POSITION
NET CONTENTS Part # LBS C.F. Liters LQ NO-USP-L1 404 3519 99,654
WARNING: RX Only Administration of Nitrous Oxide may be hazardous or contraindicated. For use only by or under the supervision of a licensed practitioner who is experienced in the use and administration of Nitrous Oxide and is familiar with the indications, effects, dosages, methods, and frequency and duration of administration, and with the hazards, contraindications and side effects, and the precautions to be taken. DANGER: MAY CAUSE OR INTENSIFY FIRE; OXIDIZER CONTAINS GAS UNDER PESSURE; MAY EXPLODE IF HEATED. MAY CUASE DROWSINESS OR DIZZINESS. MAY DISPLACE OXYGEN AND CAUSE RAPID SUFFOCATION. MAY CAUSE FROSTBITE. Do not handle until all safety precautions have been read and understood. Keep and store away from clothing and other combustible materials. Keep valves and fittings free from grease and oil. Avoid breathing gas. Do not put in eyes on skin or on clothing. Use and store only outdoors or in a well-ventilated place. In case of fire: stop leak if safe to do so. Use a back flow preventive device in the piping. Use only with equipment of compatible materials of construction and rated for cylinder pressure. Use only with equipment cleaned for oxygen service. Open valve slowly. Close valve after each use and when empty. Protect from sunlight when ambient temperature exceeds 52 degrees C (125 degrees F). Read and follow the Safety Data Sheet (SDS) before use. FIRST AID: IF INHALED: Remove person to fresh air and keep comfortable for breathing. Call a POISON CENTER or doctor/physician if you feel unwell. IF ON SKIN: Thaw frosted parts with lukewarm water. Do not rub affected area. Get immediate medical advice/attention CAS: 10024-97-2 DO NOT REMOVE THIS LABEL.